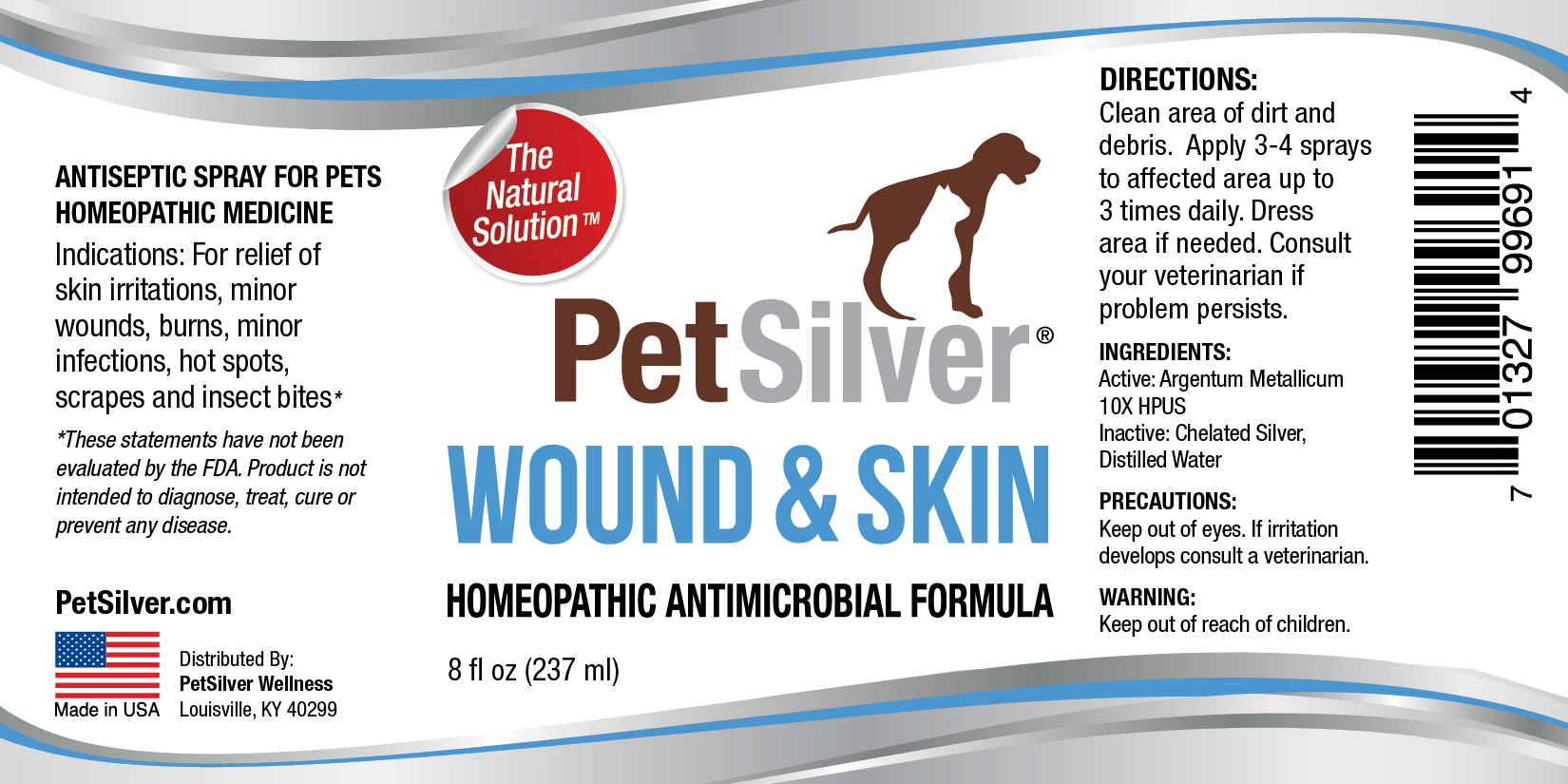 DRUG LABEL: PetSilver Wound 8
NDC: 72363-018 | Form: SPRAY
Manufacturer: AG Essence
Category: homeopathic | Type: HUMAN OTC DRUG LABEL
Date: 20251214

ACTIVE INGREDIENTS: SILVER 0.007 g/237 g
INACTIVE INGREDIENTS: WATER 235.957 g/237 g; ANHYDROUS CITRIC ACID 0.036 g/237 g

PetSilver Wound Spray 8 ounces

DIRECTIONS:

Clean area of dirt and debris. Apply 3-4 sprays to affected area up to 3 times daily. Dress area if needed. Consult your veterinarian if problem persists.

PRECAUTIONS:

out of eyes. If irritation develops consult a veterinarian.

Indications:

For relief of skin irritations, minor wounds, burns, minor infections, hot spots, scrapes and insect bites.

INGREDIENT:

Active: Argentum Metallicum10X HPUS

INGREDIENTS:

Inactive: Chelated Silver, Distilled Water

WARNING

Keep out of reach of children.

WARNING:

Keep out of reach of children